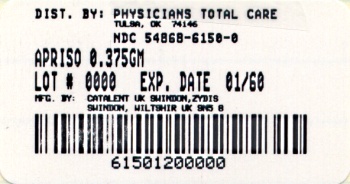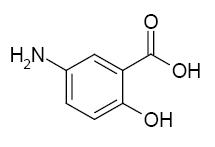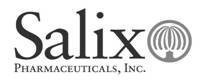 DRUG LABEL: APRISO
NDC: 54868-6150 | Form: CAPSULE, EXTENDED RELEASE
Manufacturer: Physicians Total Care, Inc.
Category: prescription | Type: HUMAN PRESCRIPTION DRUG LABEL
Date: 20120215

ACTIVE INGREDIENTS: MESALAMINE 375 mg/1 1
INACTIVE INGREDIENTS: SILICON DIOXIDE; MAGNESIUM STEARATE; CELLULOSE, MICROCRYSTALLINE; HYPROMELLOSES; METHACRYLIC ACID - METHYL METHACRYLATE COPOLYMER (1:1); TALC; TITANIUM DIOXIDE; TRIETHYL CITRATE; ASPARTAME; ANHYDROUS CITRIC ACID; POVIDONE

HIGHLIGHTS OF PRESCRIBING INFORMATION

These highlights do not include all the information needed to use APRISO safely and effectively. See full prescribing information for APRISO.
APRISO™ (mesalamine) extended-release capsules
Initial U.S. Approval: 1987

1 INDICATIONS AND USAGE

- APRISO is a locally-acting aminosalicylate indicated for the maintenance of remission of ulcerative colitis in adults (1)

2 DOSAGE AND ADMINISTRATION

- Four APRISO capsules once daily (1.5 g/day) in the morning with or without food. Do not co-administer with antacids (2)

3 DOSAGE FORMS AND STRENGTHS

- Extended-release capsules: 0.375 g (3)

4 CONTRAINDICATIONS

- Hypersensitivity to salicylates, aminosalicylates, or any component of APRISO capsules (4)

5 WARNINGS AND PRECAUTIONS

- Renal impairment may occur. Assess renal function at the beginning of treatment and periodically during therapy (5.1)
- Acute exacerbation of colitis symptoms can occur (5.2)
- Use caution with pre-existing liver disease (5.4)

6 ADVERSE REACTIONS

- The most common adverse reactions (incidence ≥3%) are headache, diarrhea, upper abdominal pain, nausea, nasopharyngitis, flu or flu-like illness, sinusitis (6.1)

To report SUSPECTED ADVERSE REACTIONS, contact Salix Pharmaceuticals, Inc. at 1-800-508-0024 or FDA at 1-800-FDA-1088 or www.fda.gov/medwatch.

7 DRUG INTERACTIONS

- Do not co-administer with antacids (7.1)

8 USE IN SPECIFIC POPULATIONS

- Use with caution in patients with renal disease (5.1)
- Monitor blood cell counts in geriatric patients (8.5)
- Advise patients with phenylketonuria that APRISO contains aspartame (17.1)

FULL PRESCRIBING INFORMATION

1 INDICATIONS AND USAGE

APRISO capsules are indicated for the maintenance of remission of ulcerative colitis in patients 18 years of age and older.

2 DOSAGE AND ADMINISTRATION

The recommended dose for maintenance of remission of ulcerative colitis in adult patients is 1.5 g (four APRISO capsules) orally once daily in the morning. APRISO may be taken without regard to meals. APRISO should not be co-administered with antacids. An evaluation of renal function is recommended before initiating therapy with APRISO.

3 DOSAGE FORMS AND STRENGTHS

Extended-release capsules containing 0.375 g mesalamine.

4 CONTRAINDICATIONS

APRISO is contraindicated in patients with hypersensitivity to salicylates or aminosalicylates or to any of the components of APRISO capsules.

5 WARNINGS AND PRECAUTIONS

5.1 Renal Impairment

Renal impairment, including minimal change nephropathy, acute and chronic interstitial nephritis, and, rarely, renal failure, has been reported in patients given products such as APRISO that contain mesalamine or are converted to mesalamine.

It is recommended that patients have an evaluation of renal function prior to initiation of APRISO therapy and periodically while on therapy. Exercise caution when using APRISO in patients with known renal dysfunction or a history of renal disease.

In animal studies, the kidney was the principal organ for toxicity [See Nonclinical Toxicology (13.2)]

5.2 Mesalamine-Induced Acute Intolerance Syndrome

Mesalamine has been associated with an acute intolerance syndrome that may be difficult to distinguish from a flare of inflammatory bowel disease. Although the exact frequency of occurrence has not been determined, it has occurred in 3% of patients in controlled clinical trials of mesalamine or sulfasalazine. Symptoms include cramping, acute abdominal pain and bloody diarrhea, sometimes fever, headache, and rash. If acute intolerance syndrome is suspected, promptly discontinue treatment with APRISO.

5.3 Hypersensitivity

Some patients who have experienced a hypersensitivity reaction to sulfasalazine may have a similar reaction to APRISO capsules or to other compounds that contain or are converted to mesalamine.

5.4 Hepatic Impairment

There have been reports of hepatic failure in patients with pre-existing liver disease who have been administered mesalamine. Caution should be exercised when administering APRISO to patients with liver disease.

6 ADVERSE REACTIONS

6.1 Clinical Studies Experience

The data described below reflect exposure to APRISO in 557 patients, including 354 exposed for at least 6 months and 250 exposed for greater than one year. APRISO was studied in two placebo-controlled trials (n = 367 treated with APRISO) and in one open-label, long-term study (n = 190 additional patients). The population consisted of patients with ulcerative colitis; the mean age was 47 years, 54% were female, and 93% were white. Patients received doses of APRISO 1.5 g administered orally once per day for six months in the placebo-controlled trials and for up to 24 months in the open-label study.

Because clinical studies are conducted under widely varying conditions, adverse reaction rates observed in the clinical trials of a drug cannot be directly compared to rates in the clinical trials of another drug and may not reflect the rates observed in practice.

In the two placebo-controlled trials, 59% of APRISO-treated patients experienced an adverse reaction compared with 64% of placebo patients. Most adverse reactions with APRISO were mild or moderate in severity. Severe adverse reactions occurred in 6% of APRISO-treated patients and 5% of placebo-treated patients. Discontinuations due to adverse reactions occurred in 11% of APRISO-treated patients and 17% of placebo-treated patients; the most common adverse reaction resulting in study discontinuation was recurrence of ulcerative colitis (APRISO 6%, placebo 14%). The most common reactions reported with APRISO (≥3%) are shown in Table 1 below.

Table 1: Treatment-Emergent Adverse Reactions during Clinical Trials Occurring in at Least 3% of APRISO-Treated Patients and at a Greater Rate than with Placebo
MedDRA Preferred Term | APRISO 1.5g/day N=367 | Placebo N=185
Headache | 11% | 8%
Diarrhea | 8% | 7%
Abdominal Pain Upper | 5% | 3%
Nausea | 4% | 3%
Nasopharyngitis | 4% | 3%
Influenza & Influenza-like illness | 4% | 4%
Sinusitis | 3% | 3%

The following adverse reactions, presented by body system, were reported at a frequency less than 3% in patients treated with APRISO for up to 24 months in controlled and open-label trials.

Ear and Labyrinth Disorders: tinnitus, vertigo

Dermatological Disorder: alopecia

Gastrointestinal: abdominal pain lower, rectal hemorrhage

Laboratory Abnormalities: increased triglycerides, decreased hematocrit and hemoglobin

General Disorders and Administration Site Disorders: fatigue

Hepatic: hepatitis cholestatic, transaminases increased

Renal Disorders: creatinine clearance decreased, hematuria

Musculoskeletal: pain, arthralgia

Respiratory: dyspnea

6.2 Adverse Reaction Information from Other Sources

The following adverse reactions have been identified during clinical trials of a product similar to APRISO and post approval use of other mesalamine-containing products such as APRISO. Because many of these reactions are reported voluntarily from a population of unknown size, it is not always possible to reliably estimate their frequency or establish a causal relationship to drug exposure.

Body as a Whole: lupus-like syndrome, drug fever

Cardiovascular: pericarditis, pericardial effusion, myocarditis

Gastrointestinal: pancreatitis, cholecystitis, gastritis, gastroenteritis, gastrointestinal bleeding, perforated peptic ulcer

Hepatic: jaundice, cholestatic jaundice, hepatitis, liver necrosis, liver failure, Kawasaki-like syndrome including changes in liver enzymes

Hematologic: agranulocytosis, aplastic anemia

Neurological/Psychiatric: peripheral neuropathy, Guillain-Barré syndrome, transverse myelitis

Respiratory/Pulmonary: eosinophilic pneumonia, interstitial pneumonitis

Skin: psoriasis, pyoderma gangrenosum, erythema nodosum

Renal/Urogenital: reversible oligospermia

7 DRUG INTERACTIONS

Based on in vitro studies, APRISO is not expected to inhibit the metabolism of drugs that are substrates of CYP1A2, CYP2C9, CYP2C19, CYP2D6, or CYP3A4.

7.1 Antacids

Because the dissolution of the coating of the granules in APRISO capsules depends on pH, APRISO capsules should not be co-administered with antacids.

8 USE IN SPECIFIC POPULATIONS

8.1 Pregnancy

Pregnancy Category B. Reproduction studies with mesalamine have been performed in rats at oral doses up to 320 mg/kg/day (about 1.7 times the recommended human dose based on a body surface area comparison) and rabbits at doses up to 495 mg/kg/day (about 5.4 times the recommended human dose based on a body surface area comparison) and have revealed no evidence of impaired fertility or harm to the fetus due to mesalamine. There are, however, no adequate and well-controlled studies in pregnant women. Because animal reproduction studies are not always predictive of human response, this drug should be used during pregnancy only if clearly needed.

Mesalamine is known to cross the placental barrier.

8.3 Nursing Mothers

Low concentrations of mesalamine and higher concentrations of its N-acetyl metabolite have been detected in human breast milk. The clinical significance of this has not been determined and there is limited experience of nursing women using mesalamine. Caution should be exercised when APRISO is administered to a nursing woman.

8.4 Pediatric Use

Safety and effectiveness of APRISO capsules in pediatric patients have not been established.

8.5 Geriatric Use

Clinical studies of APRISO did not include sufficient numbers of subjects aged 65 and over to determine whether they respond differently than younger subjects. Other reported clinical experience has not identified differences in responses between elderly and younger patients. In general, the greater frequency of decreased hepatic, renal, or cardiac function, and of concomitant disease or other drug therapy in elderly patients should be considered when prescribing APRISO.

Reports from uncontrolled clinical studies and postmarketing reporting systems suggested a higher incidence of blood dyscrasias, i.e., neutropenia, pancytopenia, in patients who were 65 years or older who were taking mesalamine-containing products such as APRISO. Caution should be taken to closely monitor blood cell counts during mesalamine therapy.

Mesalamine is known to be substantially excreted by the kidney, and the risk of adverse reactions to this drug may be greater in patients with impaired renal function. Because elderly patients are more likely to have decreased renal function, care should be taken when prescribing this drug therapy. [see Warning and Precautions (5.1)].

10 OVERDOSAGE

APRISO is an aminosalicylate, and symptoms of salicylate toxicity include hematemesis, tachypnea, hyperpnea, tinnitus, deafness, lethargy, seizures, confusion, or dyspnea. Severe intoxication may lead to electrolyte and blood pH imbalance and potentially to other organ (e.g., renal and liver) involvement. There is no specific antidote for mesalamine overdose; however, conventional therapy for salicylate toxicity may be beneficial in the event of acute overdosage. This includes prevention of further gastrointestinal tract absorption by emesis and, if necessary, by gastric lavage. Fluid and electrolyte imbalance should be corrected by the administration of appropriate intravenous therapy. Adequate renal function should be maintained. APRISO is a pH-dependent delayed-release product and this factor should be considered when treating a suspected overdose.

11 DESCRIPTION

Each APRISO capsule is a delayed- and extended-release dosage form for oral administration. Each capsule contains 0.375 g of mesalamine USP (5-aminosalicylic acid, 5-ASA), an anti-inflammatory drug. The structural formula of mesalamine is:

Molecular Weight: 153.14

Molecular Formula: C7H7NO3

Each APRISO capsule contains granules composed of mesalamine in a polymer matrix with an enteric coating that dissolves at pH 6 and above.

The inactive ingredients of APRISO capsules are colloidal silicon dioxide, magnesium stearate, microcrystalline cellulose, simethicone emulsion, ethylacrylate/methylmethacrylate copolymer nonoxynol 100 dispersion, hypromellose, methacrylic acid copolymer, talc, titanium dioxide, triethyl citrate, aspartame, anhydrous citric acid, povidone, vanilla flavor, and edible black ink.

12 CLINICAL PHARMACOLOGY

12.1 Mechanism of Action

The mechanism of action of mesalamine (5-ASA) is unknown, but appears to be local to the intestinal mucosa rather than systemic. Mucosal production of arachidonic acid metabolites, both through the cyclooxygenase pathways, i.e., prostanoids, and through the lipoxygenase pathways, i.e., leukotrienes and hydroxyeicosatetraenoic acids, is increased in patients with ulcerative colitis, and it is possible that 5-ASA diminishes inflammation by blocking production of arachidonic acid metabolites.

12.3 Pharmacokinetics

Absorption

The pharmacokinetics of 5-ASA and its metabolite, N-acetyl-5-aminosalicylic acid (N-Ac-5-ASA), were studied after a single and multiple oral doses of 1.5 g APRISO in a crossover study in healthy subjects under fasting conditions. In the multiple-dose period, each subject received APRISO 1.5 g (4 x 0.375 g capsules) every 24 hours (QD) for 7 consecutive days. Steady state was reached on Day 6 of QD dosing based on trough concentrations.

After single and multiple doses of APRISO, peak plasma concentrations were observed at about 4 hours post dose. At steady state, moderate increases (1.5-fold and 1.7-fold) in systemic exposure (AUC0-24) to 5-ASA and N-Ac-5-ASA were observed when compared with a single-dose of APRISO.

Pharmacokinetic parameters after a single dose of 1.5 g APRISO and at steady state in healthy subjects under fasting condition are shown in Table 2.

Table 2: Single Dose and Multiple Dose Mean (±SD) Plasma Pharmacokinetic Parameters of Mesalamine (5-ASA) and N-Ac-5-ASA after 1.5 g APRISO Administration in Healthy Subjects
Mesalamine (5-ASA) | Single Dose (n=24) | Multiple Dosec (n=24)
AUC0-24 (μg*h/mL) | 11 ± 5 | 17 ± 6
AUC0-inf (μg*h/mL) | 14 ± 5 | -
Cmax (μg/mL) | 2.1 ± 1.1 | 2.7 ± 1.1
Tmax (h)a | 4 (2, 16) | 4 (2, 8)
t½ (h)b | 9 ± 7 | 10 ± 8
N-Ac-5-ASA
AUC0-24 (μg*h/mL) | 26 ± 6 | 37 ± 9
AUC0-inf (μg*h/mL) | 51 ± 23 | -
Cmax (μg/mL) | 2.8 ± 0.8 | 3.4 ± 0.9
Tmax (h)a | 4 (4, 12) | 5 (2, 8)
t½ (h)b | 12 ± 11 | 14 ± 10
a Median (range); b Harmonic mean (pseudo SD); c after 7days of treatment

In a separate study (n = 30), it was observed that under fasting conditions about 32% ± 11% (mean ± SD) of the administered dose was systemically absorbed based on the combined cumulative urinary excretion of 5-ASA and N-Ac-5-ASA over 96 hours post-dose.

The effect of a high fat meal intake on absorption of mesalamine granules (the same granules contained in APRISO capsules) was evaluated in 30 healthy subjects. Subjects received 1.6 g of mesalamine granules in sachet (2 x 0.8 g) following an overnight fast or a high fat meal in a crossover study. Under fed conditions, tmax for both 5-ASA and N-Ac-5-ASA was prolonged by 4 and 2 hours, respectively. A high fat meal did not affect Cmax for 5-ASA, but a 27% increase in the cumulative urinary excretion of 5-ASA was observed with a high fat meal. The overall extent of absorption of N-Ac-5-ASA was not affected by a high fat meal. As APRISO and mesalamine granules in sachet were bioequivalent, APRISO can be taken without regard to food.

Distribution

In an in vitro study, at 2.5 μg/mL, mesalamine and N-Ac-5-ASA are 43 ± 6% and 78 ± 1% bound, respectively, to plasma proteins. Protein binding of N-Ac-5-ASA does not appear to be concentration dependent at concentrations ranging from 1 to 10 μg/mL.

Metabolism

The major metabolite of mesalamine is N-acetyl-5-aminosalicylic acid (N-Ac-5-ASA). It is formed by N-acetyltransferase activity in the liver and intestinal mucosa.

Elimination

Following single and multiple doses of APRISO, the mean half-lives were 9 to 10 hours for 5-ASA, and 12 to 14 hours for N-Ac-5-ASA. Of the approximately 32% of the dose absorbed, about 2% of the dose was excreted unchanged in the urine, compared with about 30% of the dose excreted as N-Ac-5-ASA.

In Vitro Drug-Drug Interaction Study

In an in vitro study using human liver microsomes, 5-ASA and its metabolite, N-Ac-5-ASA, were shown not to inhibit the major CYP enzymes evaluated (CYP1A2, CYP2C9, CYP2C19, CYP2D6, and CYP3A4). Therefore, mesalamine and its metabolite are not expected to inhibit the metabolism of other drugs that are substrates of CYP1A2, CYP2C9, CYP2C19, CYP2D6, or CYP3A4.

13 NONCLINICAL TOXICOLOGY

13.1 Carcinogenesis, Mutagenesis, Impairment of Fertility

Dietary mesalamine was not carcinogenic in rats at doses as high as 480 mg/kg/day, or in mice at 2000 mg/kg/day. These doses are about 2.6 and 5.4 times the recommended human dose of granulated mesalamine capsules of 1.5 g/day (30 mg/kg if 50 kg body weight assumed or 1110 mg/m^2), respectively, based on body surface area. Mesalamine was negative in the Ames test, the mouse lymphoma cell (L5178Y/TK+/-) forward mutation test, the sister chromatid exchange assay in the Chinese hamster bone marrow test, and the mouse bone marrow micronucleus test. Mesalamine at oral doses up to 320 mg/kg (about 1.7 times the recommended human dose based on body surface area) was found to have no effect on fertility or reproductive performance in rats.

13.3 Animal Toxicology and/or Pharmacology

Renal Toxicity

Animal studies with mesalamine (13-week and 26-week oral toxicity studies in rats, and 26-week and 52-week oral toxicity studies in dogs) have shown the kidney to be the major target organ of mesalamine toxicity. Oral doses of 40 mg/kg/day (about 0.20 times the human dose, on the basis of body surface area) produced minimal to slight tubular injury, and doses of 160 mg/kg/day (about 0.90 times the human dose, on the basis of body surface area) or higher in rats produced renal lesions including tubular degeneration, tubular mineralization, and papillary necrosis. Oral doses of 60 mg/kg/day (about 1.1 times the human dose, on the basis of body surface area) or higher in dogs also produced renal lesions including tubular atrophy, interstitial cell infiltration, chronic nephritis, and papillary necrosis.

Overdosage

Single oral doses of 800 mg/kg (about 2.2 times the recommended human dose, on the basis of body surface area) and 1800 mg/kg (about 9.7 times the recommended human dose, on the basis of body surface area) of mesalamine were lethal to mice and rats, respectively, and resulted in gastrointestinal and renal toxicity.

14 CLINICAL STUDIES

14.1 Ulcerative Colitis

Two similar, randomized, double-blind, placebo-controlled, multi-center studies were conducted in a total of 562 adult patients in remission from ulcerative colitis. The study populations had a mean age of 46 years (11% age 65 years or older), were 53% female, and were primarily white (92%).

Ulcerative colitis disease activity was assessed using a modified Sutherland Disease Activity Index^1 (DAI), which is a sum of four subscores based on stool frequency, rectal bleeding, mucosal appearance on endoscopy, and physician’s rating of disease activity. Each subscore can range from 0 to 3, for a total possible DAI score of 12.

At baseline, approximately 80% of patients had a total DAI score of 0 or 1.0. Patients were randomized 2:1 to receive either APRISO 1.5 g or placebo once daily in the morning for six months. Patients were assessed at baseline, 1 month, 3 months, and 6 months in the clinic, with endoscopy performed at baseline, at end of study, or if clinical symptoms developed. Relapse was defined as a rectal bleeding subscale score of 1 or more and a mucosal appearance subscale score of 2 or more using the DAI. The analysis of the intent-to-treat population was a comparison of the proportions of patients who remained relapse-free at the end of six months of treatment. For the table below (Table 3) all patients who prematurely withdrew from the study for any reason were counted as relapses.

In both studies, the proportion of patients who remained relapse-free at six months was greater for APRISO than for placebo.

Table 3: Percentage of Patients Relapse-Free* through 6 Months in APRISO Maintenance Studies
 | APRISO 1.5 g/day % (# no relapse/N) | Placebo % (# no relapse/N) | Difference (95% C.I.) | P-value
Study 1 | 68% (143/209) | 51% (49/96) | 17% (5.5, 29.2) | <0.001
Study 2 | 71% (117/164) | 59% (55/93) | 12% (0, 24.5) | 0.046
*Relapse counted as rectal bleeding score ≥ 1 and mucosal appearance score ≥ 2, or premature withdrawal from study.

Examination of gender subgroups did not identify difference in response to APRISO among these subgroups. There were too few elderly and too few African-American patients to adequately assess difference in effects in those populations.

The use of APRISO for treating ulcerative colitis beyond six months has not been evaluated in controlled clinical trials.

15 REFERENCES

1. Sutherland LR, Martin F, Greer S, Robinson M, Greenberger N, Saibil F, et al. 5-Aminosalicylic acid enema in the treatment of distal ulcerative colitis, proctosigmoiditis, and proctitis. Gastroenterology 1987;92(6):1894-1898.

16 HOW SUPPLIED/STORAGE AND HANDLING

APRISO is available as light blue opaque hard gelatin capsules containing 0.375 g mesalamine and with the letters “G” and “M” on either side of a black band imprinted on the capsule.

NDC 54868-6150-0 Bottles of 120 capsules

Storage :
Store at 20° to 25°C (68° to 77°F); excursions permitted between 15° and 30°C (59° and 86°F). See USP Controlled Room Temperature.

17 PATIENT COUNSELING INFORMATION

17.1 Patients with Phenylketonuria

- Inform patients with phenylketonuria (PKU) or their caregivers that each APRISO capsule contains aspartame equivalent to 0.56 mg of phenylalanine, so that the recommended adult dosing provides an equivalent of 2.24 mg of phenylalanine per day.

17.2 General Counseling Information

- Instruct patients not to take APRISO capsules with antacids, because it could affect the way APRISO dissolves.
- Instruct patients to contact a health care provider if they experience a worsening of ulcerative colitis symptoms, because it could be due to a reaction to APRISO.

Manufactured by:

Catalent Pharma Solutions

Manufactured for:

Salix Pharmaceuticals, Inc.

Raleigh, NC 27615

* APRISOTM is a trademark of Salix Pharmaceuticals, Inc.

© 2008 Salix Pharmaceuticals, Inc.

Product protected by U.S. Patent No. 6,551,620 and U.S. Patent No. 7,547,451

VENART-113-1

Additional barcode labeling by:

Physicians Total Care, Inc.

Tulsa, Oklahoma 74146

PACKAGE LABEL - PRINCIPAL DISPLAY PANEL - Apriso 120 Capsules, Bottle Label

NDC 54868-6150-0

APRISO™ 0.375g
(mesalamine)
EXTENDED-RELEASE CAPSULES
120 Capsules
Rx Only